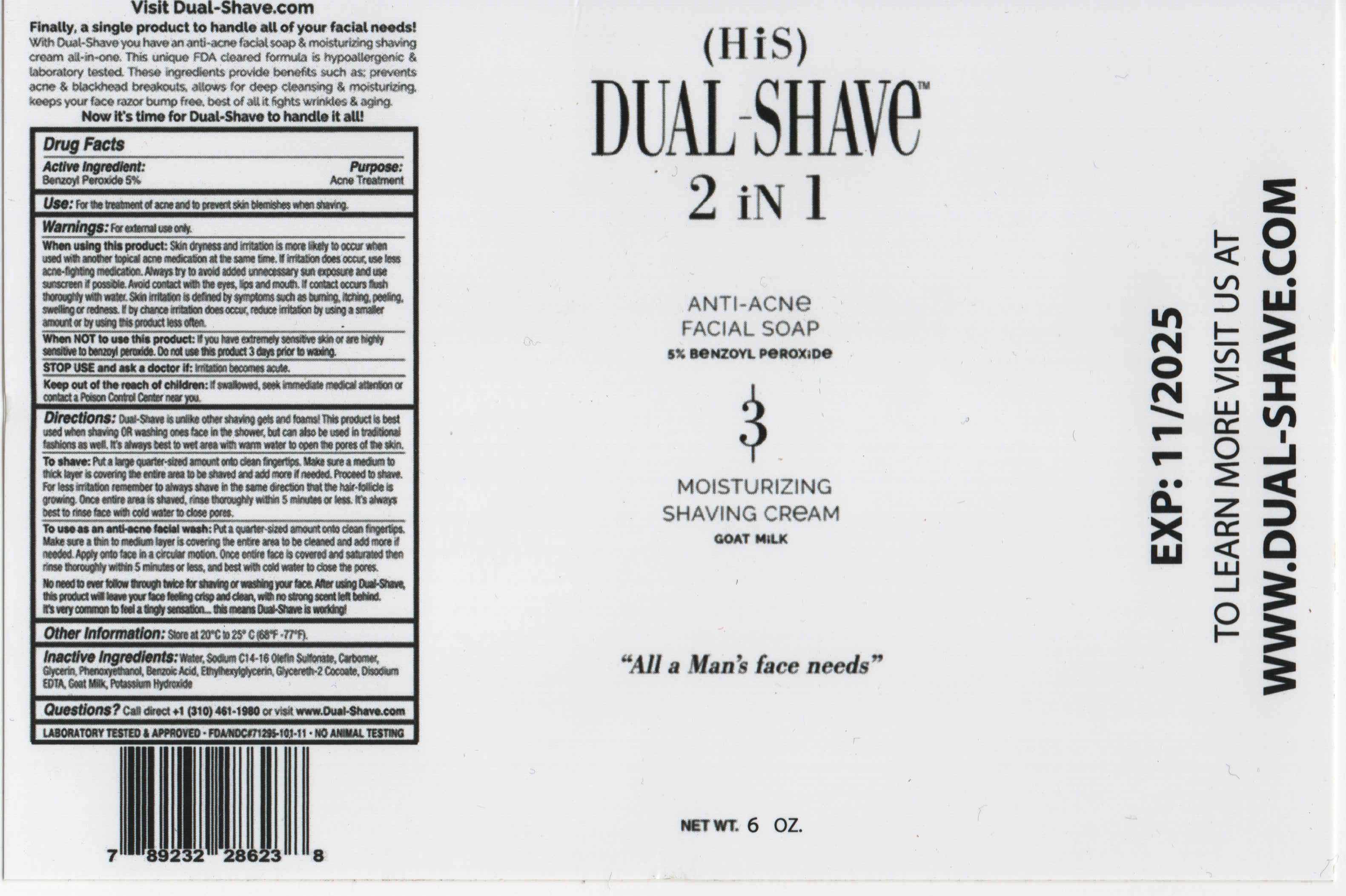 DRUG LABEL: DUAL-SHAVE 2 IN 1
NDC: 71295-101 | Form: LOTION
Manufacturer: DUAL-SHAVE LLC
Category: otc | Type: HUMAN OTC DRUG LABEL
Date: 20241217

ACTIVE INGREDIENTS: BENZOYL PEROXIDE 5 g/100 g
INACTIVE INGREDIENTS: BENZOIC ACID; ETHYLHEXYLGLYCERIN; GLYCERETH-2 COCOATE; EDETATE DISODIUM; EUCALYPTUS GLOBULUS LEAF; ZINGIBER OFFICINALE WHOLE; GAULTHERIA PROCUMBENS LEAF; AVENA SATIVA WHOLE; ALLANTOIN; GOAT MILK; WATER; MYRISTIC ACID; SODIUM C14-16 OLEFIN SULFONATE; COCAMIDOPROPYL BETAINE; STEARIC ACID; CARBOMER COPOLYMER TYPE A; POTASSIUM HYDROXIDE; LAURIC ACID; GLYCERIN; GLYCOL DISTEARATE; LAURAMINE OXIDE; SODIUM METHYL COCOYL TAURATE; PHENOXYETHANOL

DUAL-SHAVE - DUAL-SHAVE 2 IN 1 FOR HIM (71295-101)

ACTIVE INGREDIENT

BENZOYL PEROXIDE 5%

PURPOSE

ACNE TREATMENT

USE

FOR THE TREATMENT OF ACNE AND TO PREVENT SKIN BLEMISHES WHEN SHAVING.

WARNINGS

FOR EXTERNAL USE ONLY.

WHEN USING THIS PRODUCT: SKIN DRYNESS AND IRRITATION IS MORE LIKELY TO OCCUR WHEN USED WITH ANOTHER TOPICAL ACNE MEDICATION AT THE SAME TIME. IF IRRITATION DOES OCCUR, USE LESS ACNE-FIGHTING MEDICATION. ALWAYS TRY TO AVOID ADDED UNNECESSARY SUN EXPOSURE AND ALWAYS USE SUNSCREEN IF POSSIBLE. AVOID CONTACT WITH EYES, LIPS AN MOUTH. IF CONTACT OCCURS FLUSH THOROUGHLY WITH WATER. SKIN IRRITATION IS DEFINED BY SYMPTOMS SUCH AS BURNING, ITCHING, PEELING, SWELLING OR REDNESS. IF BY CHANCE IRRITATION DOES OCCUR, REDUCE IRRITATION BY USING A SMALLER AMOUNT OR BY USING THIS PRODUCT LESS OFTEN.

DO NOT USE

WHEN NOT TO USE THIS PRODUCT: IF YOU HAVE EXTREMELY SENSITIVE SKIN OR ARE HIGHLY SENSITIVE TO BENZOYL PEROXIDE.

STOP USE AND ASK A DOCTOR IF: IRRITATION BECOMES ACUTE.

KEEP OUT OF REACH OF CHILDREN: IF SWALLOWED, SEEK IMMEDIATE MEDICAL ATTENTION OR CONTACT A POISON CONTROL CENTER NEAR YOU.

DIRECTIONS

DUAL-SHAVE IS UNLIKE OTHER SHAVING GELS AND FOAMS! THIS PRODUCT IS BEST USED WHEN SHAVING OR WASHING ONES FACE IN THE SHOWER, BUT CAN ALSO BE USED IN TRADITIONAL FASHIONS AS WELL. IT'S ALWAYS BEST TO WET AREA WITH WARM WATER TO OPEN THE PORES OF THE SKIN.

TO SHAVE: PUT A LARGE QUARTER-SIZED AMOUNT ONTO CLEAN FINGERTIPS. MAKE SURE A NICE LAYER IS COVERING THE ENTIRE AREA TO BE SHAVED AND ADD MORE IF NEEDED. PROCEED TO SHAVE. FOR LESS IRRITATION REMEMBER TO ALWAYS SHAVE IN THE SAME DIRECTION THAT THE HAIR-FOLLICLE IS GROWING. ONCE THE ENTIRE AREA IS SHAVED, RINSE THOROUGHLY. IT'S ALWAYS BEST TO RINSE FACE WITH COLD WATER TO CLOSE PORES. IT'S VERY COMMON TO FEEL A TINGLY SENSATION... THIS MEANS DUAL-SHAVE IS WORKING!

TO USE AS AN ANTI-ACNE FACIAL WASH: PUT A QUARTER-SIZED AMOUNT ONTO CLEAN FINGERTIPS. MAKE SURE A NICE LAYER IS COVERING THE ENTIRE AREA TO BE CLEANED AND ADD MORE IF NEEDED. APPLY ONTO FACE IN A CIRCULAR MOTION. ONCE ENTIRE AREA IS COVERED AND SATURATED THEN RINSE WELL WITH COLD WATER TO CLOSE PORES.

NO NEED TO EVER FOLLOW THROUGH TWICE FOR SHAVING OR WASHING YOUR FACE. AFTER USING DUAL-SHAVE, THIS PRODUCT WILL LEAVE YOUR FACE FEELING CRISP AND CLEAN, WITH NO STRONG SCENT LEFT BEHIND.

OTHER INFORMATION

STORE AT 20°C TO 25°C (68°F - 77°F).

INACTIVE INGREDIENTS

WATER, MYRISTIC ACID, SODIUM C14-16 OLEFIN SULFONATE, COCAMIDOPROPYL BETAINE, STEARIC ACID, ACRYLATES COPOLYMER, POTASSIUM HYDROXIDE, LAURIC ACID, GLYCERIN, GLYCOL DISTEARATE, LAURAMINE OXIDE, SODIUM METHYL COCOYL TAURATE, PHENOXYETHANOL, BENZOIC ACID, ETHYLHEXYLGLYCERIN, GLYCERETH-2 COCOATE, FRAGRANCE, DISODIUM EDTA, EUCALYPTUS GLOBULUS LEAF EXTRACT, ZINGIBER OFFICINALE (GINGER) ROOT EXTRACT, GAULTHERIA PROCUMBENS (WINTERGREEN) LEAF EXTRACT, AVENA SATIVA (OAT) KERNEL EXTRACT, ALLANTOIN, GOAT MILK

QUESTIONS?

CALL DIRECT +1 (310) 461-1980 OR VISIT WWW.DUAL-SHAVE.COM